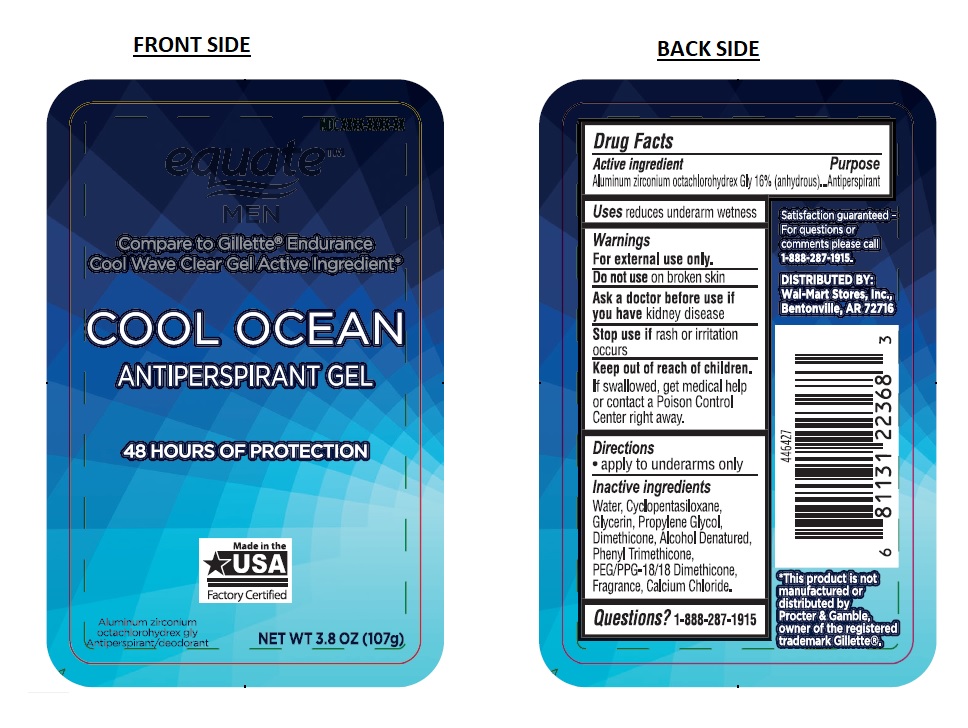 DRUG LABEL: equate MEN COOL OCEAN ANTIPERSPIRANT
NDC: 49035-144 | Form: GEL
Manufacturer: Wal-mart Stores, Inc.
Category: otc | Type: HUMAN OTC DRUG LABEL
Date: 20171207

ACTIVE INGREDIENTS: ALUMINUM ZIRCONIUM OCTACHLOROHYDREX GLY 0.16 g/1 g
INACTIVE INGREDIENTS: WATER; CYCLOMETHICONE 5; GLYCERIN; PROPYLENE GLYCOL; DIMETHICONE; ALCOHOL; PHENYL TRIMETHICONE; PEG/PPG-18/18 DIMETHICONE; CALCIUM CHLORIDE

equate MEN COOL OCEAN ANTIPERSPIRANT

Active ingredient

Aluminum zirconium octachlorohydrex Gly 16% (anhydrous)

Purpose

Antiperspirant

Uses

reduces underarm wetness

Warnings

For external use only.
Do not use on broken skin
Ask a doctor before use if you have kidney disease
Stop use if rash or irritation occurs

Keep out of reach of children.

If swallowed, get medical help or contact a Poison Control Center right away.

Directions

• apply to underarms only

Inactive ingredients

Water, Cyclopentasiloxane, Glycerin, Propylene Glycol, Dimethicone, Alcohol Denatured, Phenyl Trimethicone, PEG/PPG-18/18 Dimethicone, Fragrance, Calcium Chloride.

Questions?

1-888-287-1915

ComparetoGillette®EnduranceCoolWaveClearGelActiveIngredient*

48 HOURS OF PROTECTION

Made in the USA Factory Certified

Aluminum zirconium octachlorohydrex gly Antiperspirant/deodorant

Satisfaction guaranteed- For questions or comments please call 1-888-287-1915.

DISTRIBUTED BY:
Wal-Mart Stores, Inc., Bentonville, AR 72716

*This product is not manufactured or distributed by Procter & Gamble, owner of the registered trademark Gillette®.